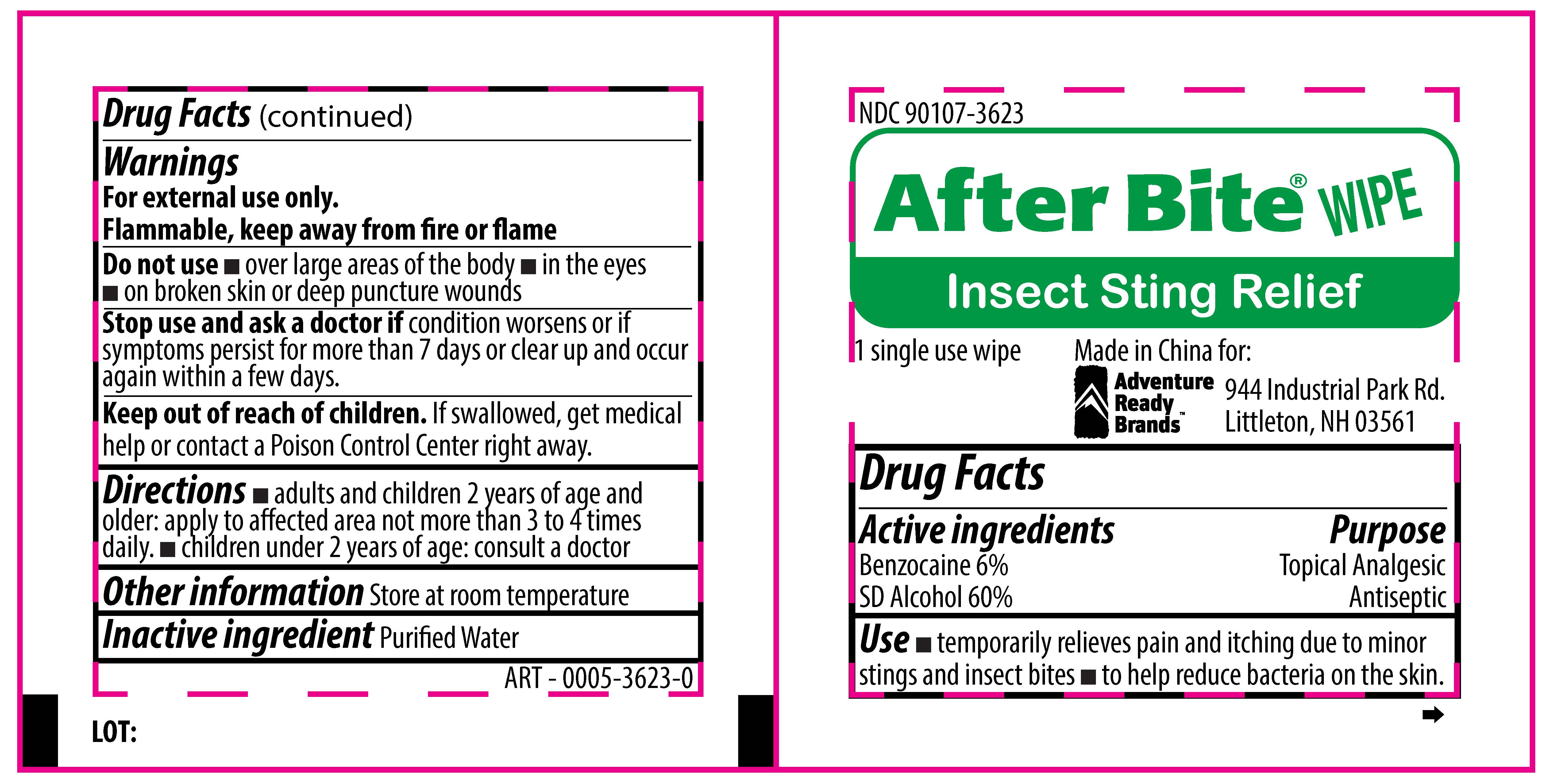 DRUG LABEL: After Bite Wipe Insect Sting Relief
NDC: 90107-3623 | Form: SWAB
Manufacturer: Adventure Ready Brands
Category: otc | Type: HUMAN OTC DRUG LABEL
Date: 20201210

ACTIVE INGREDIENTS: BENZOCAINE 6 mg/100 mg; ALCOHOL 60 mg/100 mg
INACTIVE INGREDIENTS: WATER

After Bite Wipe Insect Sting Relief

Active Ingredients

Benzocaine, 6%

SD alcohol, 60%

Purpose

Topical Analgesic
Antiseptic

Use

- temporarily relieves pain and itching due to minor stings and insect bites
- to help reduce bacteria on the skin

Warnings

For external use only.

Flammable, keep away from fire or flame.

Do not use

- over large areas of the body
- in the eyes
- on broken skin or deep puncture wounds

Stop use and ask a doctor if

condition worsens or if symptoms persist for more than 7 days or clear up and occur again within a few days.

Keep out of reach of children

If swallowed, get medical help or contact a Poison Control Center right away.

Directions

- adults and children 2 year of age and older: apply to affected area not more than 3 to 4 times daily.
- children under 2 years of age: consult a doctor

Other information

Store at room temperature

Inactive Ingredient

Purified water